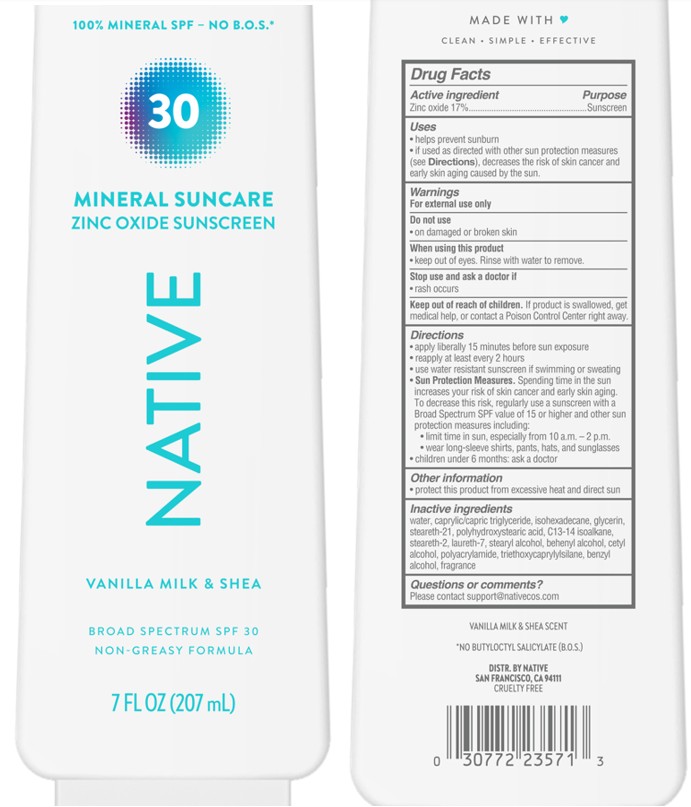 DRUG LABEL: Native Mineral Suncare Zinc Oxide Sunscreen Vanilla Milk and Shea Broad Spectrum SPF 30
NDC: 64412-5512 | Form: LOTION
Manufacturer: Twincraft Inc.
Category: otc | Type: HUMAN OTC DRUG LABEL
Date: 20251217

ACTIVE INGREDIENTS: ZINC OXIDE 17 g/100 mL
INACTIVE INGREDIENTS: POLYACRYLAMIDE (1300000 MW); STEARETH-21; WATER; GLYCERIN; BEHENYL ALCOHOL; CETYL ALCOHOL; POLYHYDROXYSTEARIC ACID (2300 MW); CAPRYLIC/CAPRIC TRIGLYCERIDE; BENZYL ALCOHOL; ISOHEXADECANE; STEARYL ALCOHOL; C13-14 ISOPARAFFIN; STEARETH-2; LAURETH-7; TRIETHOXYCAPRYLYLSILANE

Native Mineral Suncare Zinc Oxide Sunscreen Vanilla Milk and Shea Broad Spectrum SPF 30

Drug Facts

ACTIVE INGREDIENT

ZINC OXIDE 17%

PURPOSE

Sunscreen

Uses

- helps prevent sunburn
- if used as directed with other sun protection measures (see Directions), decreases the risk of skin cancer and early skin aging caused by the sun

Warnings

For external use only

Do not use

- on damaged or broken skin

When using this product

- keep out of eyes. Rinse with water to remove.

Stop use and ask a doctor if

- rash occurs

Keep out of reach of children.If product is swallowed, get medical help or contact a Poison Control Center right away.

Directions

- apply liberally 15 minutes before sun exposure
- reapply at least every 2 hours
- use water resistant sunscreen if swimming or sweating
- Sun Protection Measures.Spending time in the sun increases your risk of skin cancer and early skin aging. To decrease this risk, regularly use a sunscreen with a Broad Spectrum SPF value of 15 or higher and other sun protection measures including:
  - limit time in sun, especially from 10 a.m. – 2 p.m.
  - wear long-sleeved shirts, pants, hats, and sunglasses
- children under 6 months: ask a doctor

Other information

- protect this product from excessive heat and direct sun

Inactive ingredients

Water, caprylic/capric triglyceride, isohexadecane, glycerin, steareth-21, polyhydroxystearic acid, C13-14 isoalkane, steareth-2, laureth-7, stearyl alcohol, behenyl alcohol, cetyl alcohol, polyacrylamide, triethoxycaprylylsilane, benzyl alcohol, fragrance

Distr. by Native San Francisco, CA 94111

Questions or comments?

Please contact support@nativecos.com

PRINCIPAL DISPLAY PANEL - 207 mL Bottle

30

MINERAL SUNCARE

ZINC OXIDE SUNSCREEN

NATIVE

VANILLA MILK & SHEA

BROAD SPECTRUM SPF 30

7 FL OZ (207 mL)